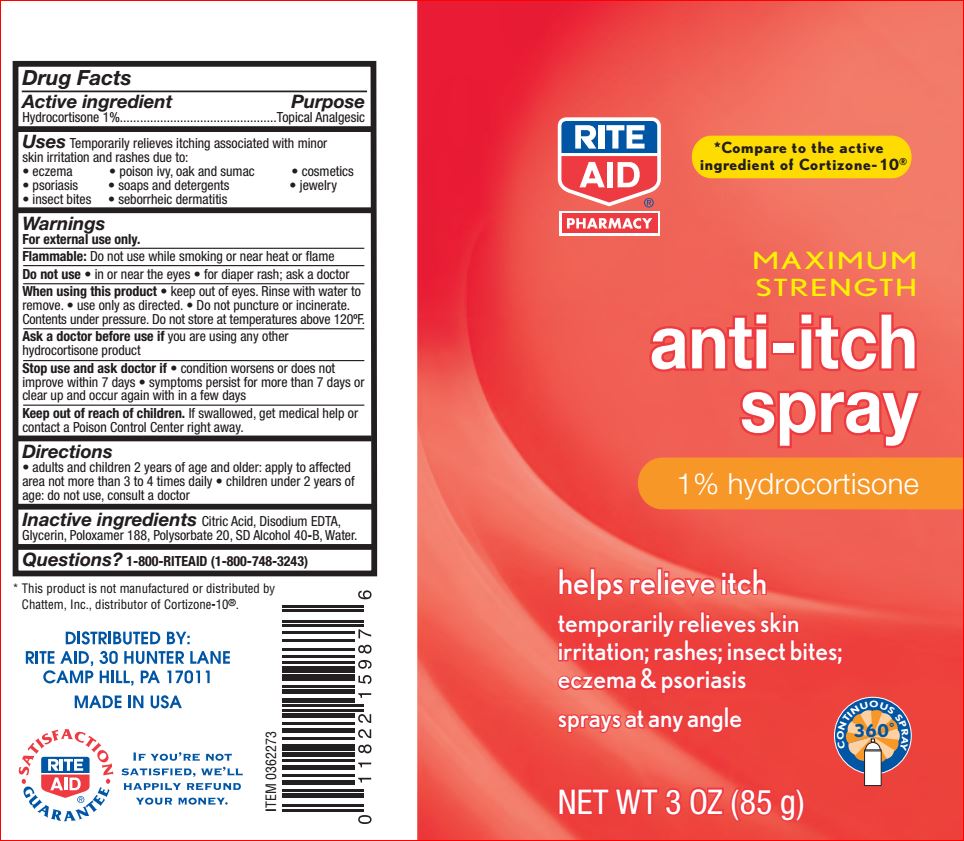 DRUG LABEL: Cooling Itch Relief
NDC: 11822-1223 | Form: SPRAY
Manufacturer: Rite Aid
Category: otc | Type: HUMAN OTC DRUG LABEL
Date: 20180612

ACTIVE INGREDIENTS: Hydrocortisone 1 g/100 g
INACTIVE INGREDIENTS: CITRIC ACID MONOHYDRATE; EDETATE DISODIUM; Glycerin; Poloxamer 188; Polysorbate 20; ALCOHOL; Water

Drug Facts

Active ingredient Purpose

Hydrocortisone - 1.00% Anti-itch

Uses

Temporarily relieves itching associated with minorskin irritation and rashes due to:

• eczema • poison ivy, oak and sumac • cosmetics

• psoriasis • soaps and detergents • jewelry

• insect bites • seborrheic dermatitis

Warnings

For external use only

Do not use

• in or near the eyes • for diaper rash: ask a doctor

When using this product

• Keep out of eyes. Rinse with water to remove • Use only as directed. • Do not puncture or incinerate. Contents under pressure
• Do not store at temperature above 120F

Stop use and ask a doctor if

• condition worsens or does not improve withing 7 days
• symptomspersist more than 7 days or clear up and occur again within a few days

Keep out of reach of the children

If swallowed, get medical help or contact a Poison Control Center right away

Directions

• adults and children 2 years of age and older: apply to affected area, not more than 3 to 4 times daily
• children under 2 years of age: ask a doctor

Inactive ingredients

Citric Acid, Disodium EDTA, Glycerin, Poloxamer 188, Polysorbate 20, SD Alcohol 40-B, Water